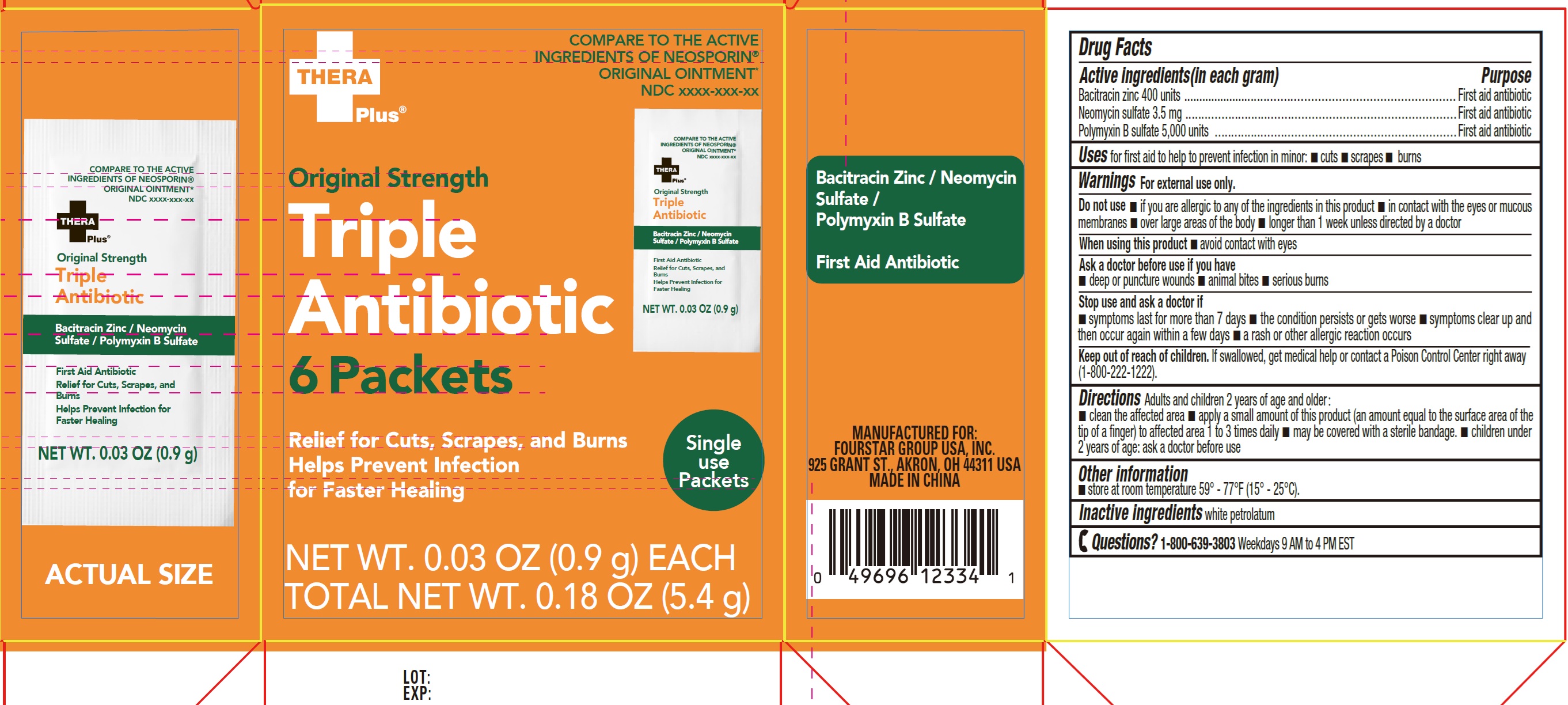 DRUG LABEL: Thera Plus Original Strength Triple Antibiotic
NDC: 80684-198 | Form: OINTMENT
Manufacturer: Fourstar Group USA, Inc
Category: otc | Type: HUMAN OTC DRUG LABEL
Date: 20251202

ACTIVE INGREDIENTS: BACITRACIN ZINC 400 U/1 g; NEOMYCIN SULFATE 3.5 mg/1 g; POLYMYXIN B SULFATE 5000 U/1 g
INACTIVE INGREDIENTS: WHITE PETROLATUM

Thera Plus Original Strength Triple Antibiotic

Active ingredients (in each gram)

Bacitracin zinc 400 units
Neomycin sulfate 3.5 mg
Polymyxin B sulfate 5,000 units

Purpose

First aid antibiotic

Uses

for first aid to help to prevent infection in minor: • cuts • scrapes • burns

Warnings

For external use only.

Do not use

• if you are allergic to any of the ingredients in this product • in contact with the eyes or mucous membranes • over large areas of the body • longer than 1 week unless directed by a doctor

When using this product

avoid contact with eyes

Ask a doctor before use if you have

• deep or puncture wounds • animal bites • serious burns

Stop use and ask a doctor if

• symptoms last for more than 7 days • the conditions persists or gets worse • symptoms clear up and the occur again within a few days • a rash or other allergic reaction occurs

Keep out of reach of children.

If swallowed, get medical help or contact a Poison Control Center right away (1-800-222-1222).

Directions

• Adults and children 2 years of age and older: • clean the affected area • apply a small amount of this product (an amount equal to the surface area of the tip of a finger) to affected area 1 to 3 times daily • may be covered with a sterile bandage. • children under 2 years of age: ask a doctor before use

Other information

• store at room temperature 59°- 77° F (15°-25°C).

Inactive ingredients

white petrolatum

Questions?

1-800-639-3803Weekdays 9 AM to 4 PM EST